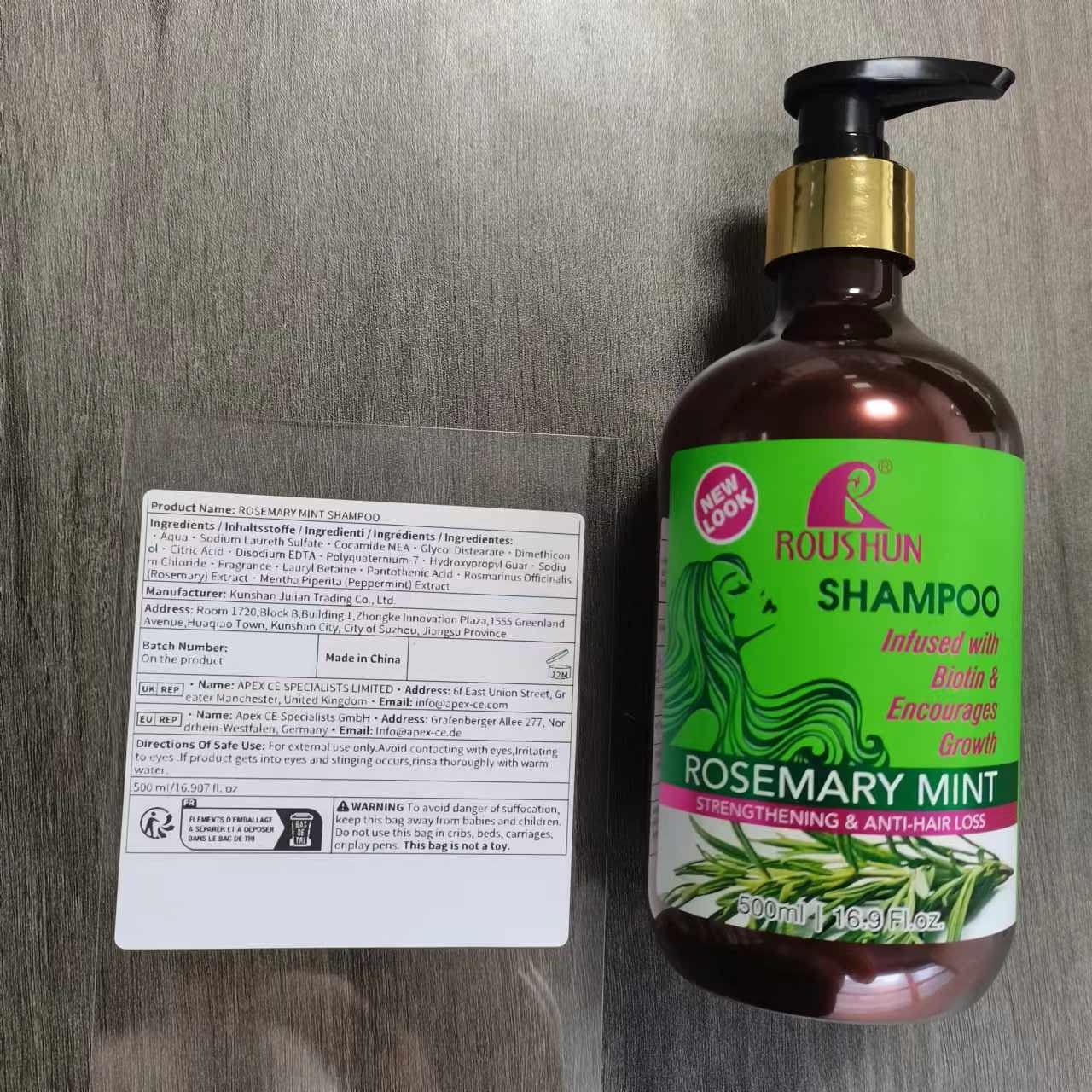 DRUG LABEL: ROSEMARY MINT
NDC: 84551-013 | Form: SHAMPOO
Manufacturer: Kunshan Julian Trading Co., Ltd.
Category: otc | Type: HUMAN OTC DRUG LABEL
Date: 20241013

ACTIVE INGREDIENTS: ROSEMARY 3 g/100 g
INACTIVE INGREDIENTS: WATER 85 g/100 g

ACTIVE INGREDIENT

Rosmarinus Officinalis (Rosemary) Extract 3%

PURPOSE

infused with biotin Encourages growth
strengthening anti-hair loss

USAGE

If used daily, it can strengthen anti-hair loss and make hair look thick.

KEEP OUT OF REACH OF CHILDREN

If swallowed,get medical help or contact a Poison Control Center right away.

DO NOT USE

on damaged or broken skin.

Stop use and ask a doctor if

rash occurs

When using this product

keep out of eyes.rinse with water to remove.

WARNINGS

For extermal use only

DOSAGE & ADMINSTRATION

BID, 5-10g per dose
Ext.

Inactive ingredient

water